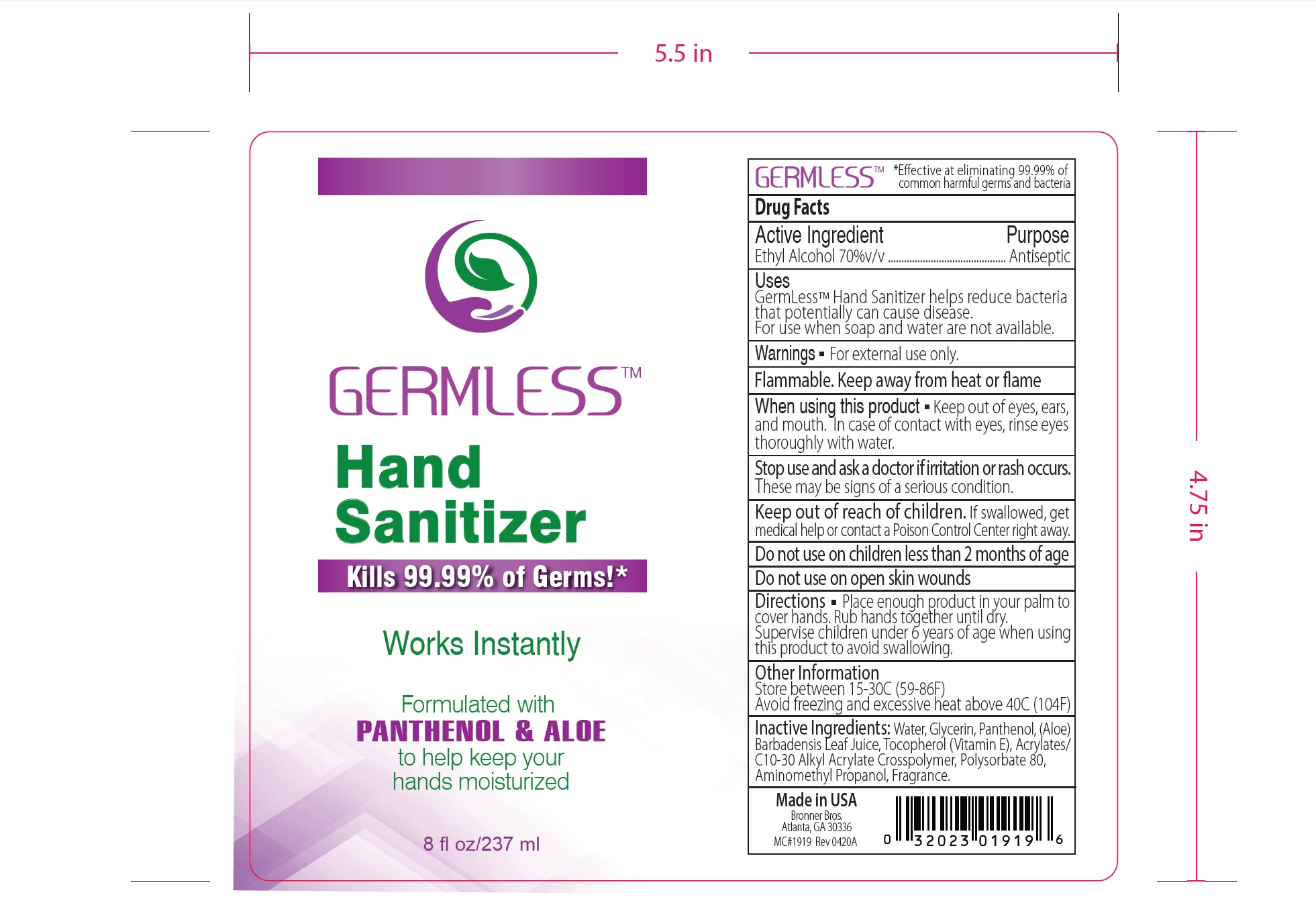 DRUG LABEL: Hand Sanitizer
NDC: 74039-237 | Form: GEL
Manufacturer: Bronner Bros., Inc.
Category: otc | Type: HUMAN OTC DRUG LABEL
Date: 20220113

ACTIVE INGREDIENTS: ALCOHOL 155.709 mL/237 mL
INACTIVE INGREDIENTS: TOCOPHEROL 0.0237 mL/237 mL; GLYCERIN 1.185 mL/237 mL; ALOE VERA LEAF 0.237 mL/237 mL; WATER; PANTHENOL 0.5925 mL/237 mL

Topical hand sanitizer, 70% ethanol vol/vol.

This is a hand sanitizer manufactured to be 70% ethanol vol/vol.

Active Ingredient(s)

Alcohol 70% v/v. Purpose: Antiseptic

Purpose

Antiseptic, Hand Sanitizer

Use

Hand Sanitizer to help reduce bacteria that potentially can cause disease. For use when soap and water are not available.

Warnings

For external use only. Flammable. Keep away from heat or flame

Do not use

- in children less than 2 months of age
- on open skin wounds

When using this product keep out of eyes, ears, and mouth. In case of contact with eyes, rinse eyes thoroughly with water.
Stop use and ask a doctor if irritation or rash occurs. These may be signs of a serious condition.
Keep out of reach of children. If swallowed, get medical help or contact a Poison Control Center right away.

Stop use and ask a doctor if irritation or rash occurs. These may be signs of a serious condition.

Keep out of reach of children. If swallowed, get medical help or contact a Poison Control Center right away.

Directions

- Place enough product on hands to cover all surfaces. Rub hands together until dry.
- Supervise children under 6 years of age when using this product to avoid swallowing.

Other information

- Store between 15-30C (59-86F)
- Avoid freezing and excessive heat above 40C (104F)

Inactive ingredients

glycerin, aloe vera, , panthanol, purified water USP

Package Label - Principal Display Panel

237 mL NDC: 74039-237-12